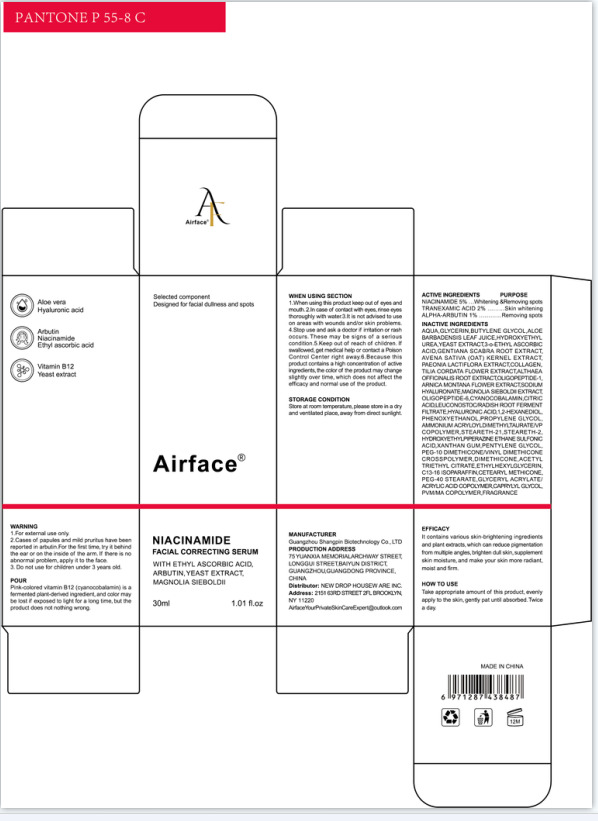 DRUG LABEL: Airface Nicotinamide Facial Correcting Serum
NDC: 84581-002 | Form: LIQUID
Manufacturer: GUANGZHOU SHANGPIN BIOTECHNOLOGY CO.,LTD
Category: otc | Type: HUMAN OTC DRUG LABEL
Date: 20240725

ACTIVE INGREDIENTS: ALPHA-ARBUTIN 1 g/100 mL; NIACINAMIDE 5 g/100 mL; TRANEXAMIC ACID 2 g/100 mL
INACTIVE INGREDIENTS: FRAGRANCE FRESH CITRUS FLORAL ORC1501495; COLLAGEN ALPHA-1(I) CHAIN BOVINE; ALOE VERA LEAF; OAT; WATER; GLYCERIN; BUTYLENE GLYCOL; HYDROXYETHYL UREA; DIMETHICONE; PENTYLENE GLYCOL; AMMONIUM ACRYLOYLDIMETHYLTAURATE/VP COPOLYMER; ARNICA MONTANA FLOWER; HYALURONATE SODIUM; STEARETH-21; HYALURONIC ACID; HYDROXYETHYLPIPERAZINE ETHANE SULFONIC ACID; C13-16 ISOPARAFFIN; GLYCERYL ACRYLATE/ACRYLIC ACID COPOLYMER (300000 CP AT 2%); STEARETH-2; ALTHAEA OFFICINALIS ROOT; PHENOXYETHANOL; 1,2-HEXANEDIOL; ACETYLTRIETHYL CITRATE; ETHYLHEXYLGLYCERIN; GENTIANA SCABRA ROOT; LEUCONOSTOC/RADISH ROOT FERMENT FILTRATE; CAPRYLYL GLYCOL; PONCEAU 4R; CYANOCOBALAMIN; TILIA CORDATA FLOWER; METHYL VINYL ETHER AND MALEIC ANHYDRIDE COPOLYMER (1100000 WAMW); CETEARYL METHICONE (15000 MW); OLIGOPEPTIDE-10; YEAST; PROPYLENE GLYCOL; PEG-40 MONOSTEARATE; XANTHAN GUM; 3-O-ETHYL ASCORBIC ACID; CITRIC ACID MONOHYDRATE

84251-002

Active Ingredient(s)

NIACINAMIDE 5%

TRANEXAMIC ACID 2%

ALPHA-ARBUTIN 1%

Purpose

①Whitening &Removing spots ②Skin whitening ③Removin. spots

Use

Take appropriate amount of this product, evenly apply to the skin, gently pat until absorbed. Twice a day.

Warnings

1.For external use only.
2.Cases of papules and mild pruritus have been reported in arbutin.For the first time, try it behind
the ear or on the inside of the arm. If there is no abnormal problem, apply it to the face.
3. Do not use for children under 3 years old.

Do not use

Donnotuse on da maged skin(cuts, abrasionseczema, sunburn)f you are allergic to any of the ingredients in this product.

WHEN USING

1.When using this product keep out of eyes and mouth.

2.In case of contact with eyes, rinse eyes thoroughly with water:

3.It is not advised to use on areas with wounds and/or skin problems.
4.Stop use and ask a doctor if iritation or rash occurs. These may be signs of a serious condition.

5. Keep out of reach of children. If swallowed, get medical help or contact a Poison Control Center right away.

6.Because this product contains a high concentration of active ingredients, the color of the product may change
slightly over time, which does not affect the efficacy and normal use of the product.

Stop use and ask a doctor if irritation or rash occurs.

KEEP OUT OF REACH OF CHILDREN

If swallowed, get medical help or contact a Poison Control Center right away.

Directions

Take appropriate amount of this product, evenly apply to the skin, gently pat until absorbed. Twice a day.

Other information

Store at room temperature, please store in a dry and ventilated place, away from direct sunlight.

Inactive ingredients

AQUA,GLYCERIN.BUTYLENE GLYCOL ,ALOE BARBADENSIS LEAF JUICE,HYDROXYETHYL
UREA,YEAST EXTRACT,3-0-ETHYL ASCORBIC ACID,GENTIANA SCABRA ROOT EXTRACT,
AVENA SATIVA (OAT) KERNEL EXTRACT, PAEONIA LACTIFLORA EXTRACT,COLLAGEN,
TILIA CORDATA FLOWER EXTRACT,ALTHAEA OFFICINALIS ROOT EXTRACT,OL IGOPEPTIDE-1.
ARNICA MONTANA FLOWER EXTRACTSODIUM HYALURONATE,MAGNOLIA SIEBOLDII EXTRACT,
OLIGOPEPTIDE- 6,CYANOCOBAL AMIN,CITRIC ACID,LEUCONOSTOCRADISH ROOT FERMENT
FILTRATE,HYALURONIC ACID,1,2-HEXANEDIOL, PHENOXYETHANOL,PROPYLENE GLYCOL,
AMMONIUM ACRYLOYLDIME THYLTAURATE/VP COPOLYMER,STEARETH-21,STEARETH-2, .
HYDROXYETHYLPIPERAZINE ETHANE SULFONIC ACID,XANTHAN GUM,PENTYLENE GLYCOL,
PEG-10 DIMETHICONEMINYL DIMETHICONE CROSSPOLYMER,DIMETHICONE , ACETYL
TRIETHYL CITRATE,ETHYLHEXYLGLYCERIN, C13-16 ISOPARAFFIN,CETEARYL METHICONE,
PEG-40 STEARATE ,GLYCERYL ACRYLATE/ ACRYLIC ACID COPOLYMER,CAPRYLYL GLYCOL,
PVM/MA COPOLYMER,FRAGRANCE